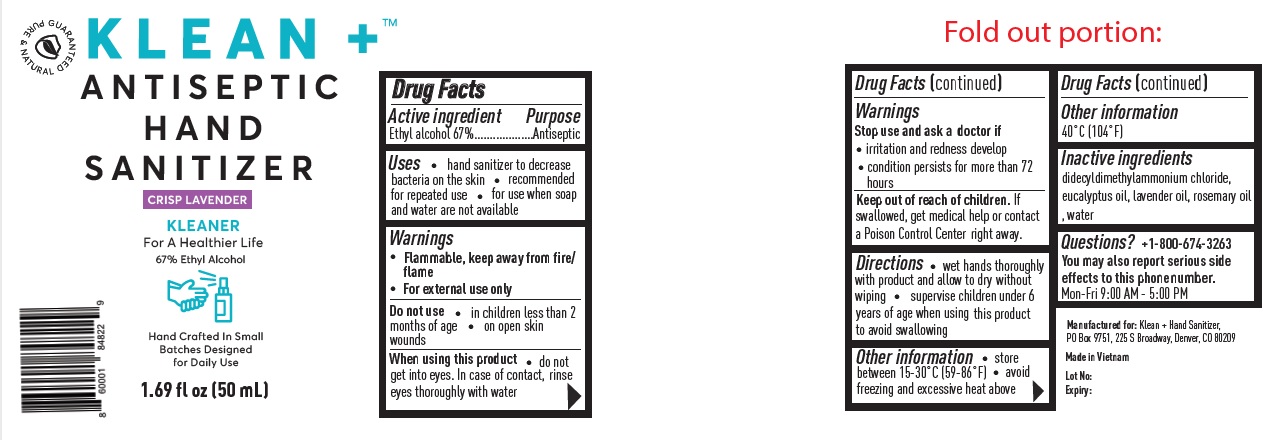 DRUG LABEL: Klean Antiseptic Hand Sanitizer
NDC: 74025-777 | Form: SPRAY
Manufacturer: CATCHERS INTERNATIONAL LIMITED LIABILITY COMPANY
Category: otc | Type: HUMAN OTC DRUG LABEL
Date: 20200328

ACTIVE INGREDIENTS: ALCOHOL 0.67 mL/1 mL
INACTIVE INGREDIENTS: DIDECYLDIMONIUM CHLORIDE; EUCALYPTUS OIL; LAVENDER OIL; ROSEMARY OIL; WATER

Klean + Antiseptic Hand Sanitizer

Active ingredient

Ethyl alcohol 67%

Purpose

Antiseptic

INDICATIONS AND USAGE

Uses • hand sanitizer to decrease bacteria on the skin • recommended for repeated use • for use when soap and water are not available

Warnings

• Flammable, keep away from fire/flame

• For external use only

Do not use • in children less than 2 months of age • on open skin wounds

When using this product • do not get into eyes. In case of contact, rinse eyes thoroughly with water

Stop use and ask a doctor if • irritation and redness develop • condition persists for more than 72 hours

Keep out of reach of children. If swallowed, get medical help or contact a Poison Control Center right away

DOSAGE AND ADMINISTRATION

Directions • wet hands thoroughly with product and allow to dry without wiping • supervise children under 6 years of age when using this product to avoid swallowing

Other information • store between 15-30°C (59-86°F) • avoid freezing and excessive heat above 40C (104F)

INACTIVE INGREDIENT

Inactive ingredients didecyldimethylammonium chloride, eucalyptus oil, lavender oil, rosemary oil, water

Questions? +1-800-674-3263

You may also report serious effects to this phone number. Mon-Fri 9:00 AM - 5:00 PM

GUARANTEED NATURAL & PURE

CRISP LAVENDER

KLEANER

For A Healthier Life

67% Ethyl Alcohol

Hand Crafted In Small Batches Designed for Daily Use

Manufactured for: Klean + Hand Sanitizer, PO Box 9751, 225 S Broadway, Denver, CO 80209

Made in Vietnam